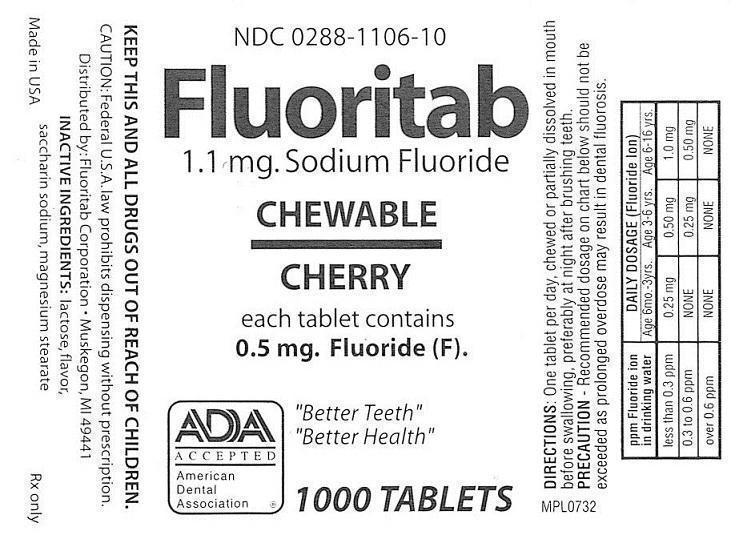 DRUG LABEL: FLUORITAB CHEWABLE
NDC: 0288-1106 | Form: TABLET, CHEWABLE
Manufacturer: Fluoritab Corporation
Category: prescription | Type: HUMAN PRESCRIPTION DRUG LABEL
Date: 20121029

ACTIVE INGREDIENTS: SODIUM FLUORIDE 0.5 mg/1 1
INACTIVE INGREDIENTS: LACTOSE; SACCHARIN SODIUM ANHYDROUS; MAGNESIUM STEARATE

ACTIVE INGREDIENT

CONTAINS: 1.1 MG SODIUM FLUORIDE

EACH TABLET CONTAINS 0.5 MG FLUORIDE

KEEP OUT OF REACH OF CHILDREN

KEEP THIS AND ALL DRUGS OUT OF REACH OF CHILDREN.

WARNINGS

CAUTION: FEDERAL (U.S.A.) LAW PROHIBITS DISPENSING WITHOUT PRESCRIPTION.

INDICATIONS AND USAGE

DIRECTIONS: ONE TABLET PER DAY, CHEWED OR PARTIALLY DISSOLVED IN MOUTH BEFORE SWALLOWING, PREFERABLY AT NIGHT AFTER BRUSHING TEETH.

INACTIVE INGREDIENT

INACTIVE INGREDIENTS: LACTOSE, FLAVOR, SACCHARIN SODIUM, MAGNESIUM STEARATE

WARNINGS AND PRECAUTIONS

PRECAUTION -RECOMMEND DOSAGE ON CHART BELOW SHOULD NOT BE EXCEEDED AS PROLONGED OVERDOSE MAY RESULT IN DENTAL FLUOROSIS.